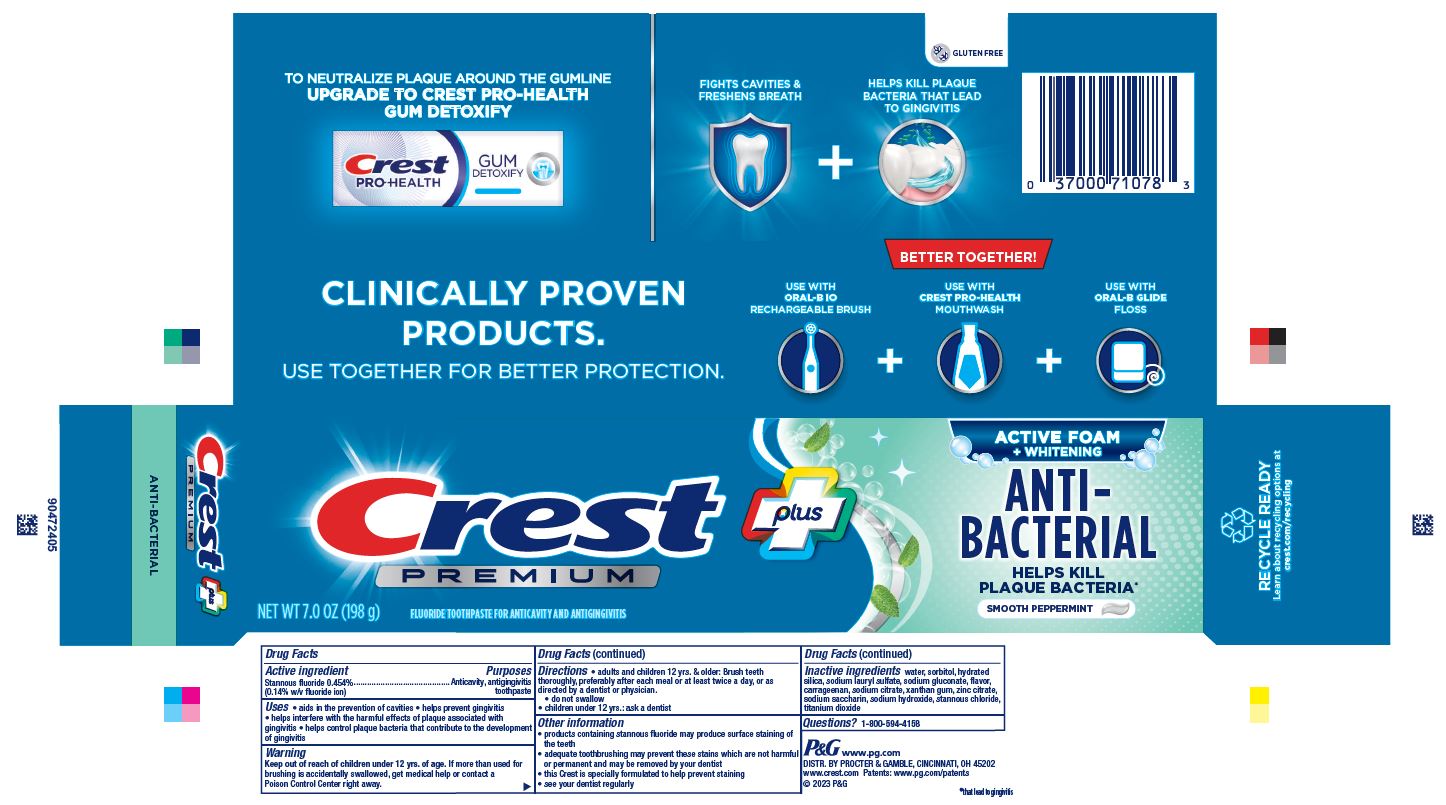 DRUG LABEL: Crest Premium Plus
NDC: 37000-992 | Form: PASTE, DENTIFRICE
Manufacturer: The Procter & Gamble Manufacturing Company
Category: otc | Type: HUMAN OTC DRUG LABEL
Date: 20250114

ACTIVE INGREDIENTS: STANNOUS FLUORIDE 1.4 mg/1 g
INACTIVE INGREDIENTS: HYDRATED SILICA; SORBITOL; SODIUM CITRATE; ZINC CITRATE; WATER; SODIUM LAURYL SULFATE; SODIUM GLUCONATE; CARRAGEENAN; SACCHARIN SODIUM; XANTHAN GUM; SODIUM HYDROXIDE; STANNOUS CHLORIDE; TITANIUM DIOXIDE

Crest Premium Plus Anti-Bacterial

Drug Facts

Active ingredient

Stannous fluoride 0.454% (0.14% w/v fluoride ion)

Purposes

Anticavity, antigingivitis toothpaste

Uses

- aids in the prevention of cavities
- helps prevent gingivitis
- helps interfere with the harmful effects of plaque associated with gingivitis
- helps control plaque bacteria that contribute to the development of gingivitis

Warnings

Keep out of reach of children. If more than used for brushing is accidentally swallowed, get medical help or contact a Poison Control Center right away.

Directions

- adults and children 12 yrs. & older: Brush teeth thoroughly, preferably after each meal or at least twice a day, or as directed by a dentist or physician.
- do not swallow
- children under 12 yrs.: ask a dentist

Other information

- products containing stannous fluoride may produce surface staining of the teeth
- adequate toothbrushing may prevent these stains which are not harmful or permanent and may be removed by your dentist
- this Crest is specially formulated to help prevent staining
- see your dentist regularly

Inactive ingredients

water, sorbitol, hydrated silica, sodium lauryl sulfate, sodium gluconate, flavor, carrageenan, sodium citrate, xanthan gum, zinc citrate, sodium saccharin, sodium hydroxide, stannous chloride, titanium dioxide

Questions?

1-800-594-4158

DISTR. BY PROCTER & GAMBLE,
CINCINNATI, OH 45202

PRINCIPAL DISPLAY PANEL - 144 g Tube Carton

Crest® plus PREMIUM

FLUORIDE TOOTHPASTE FOR ANTICAVITY AND ANTIGINGIVITIS

NET WT 7.0 OZ (198 g)

ACTIVE FOAM +WHITENING

ANTI-BACTERIAL

HELPS KILL PLAQUE BACTERIA*

smooth peppermint